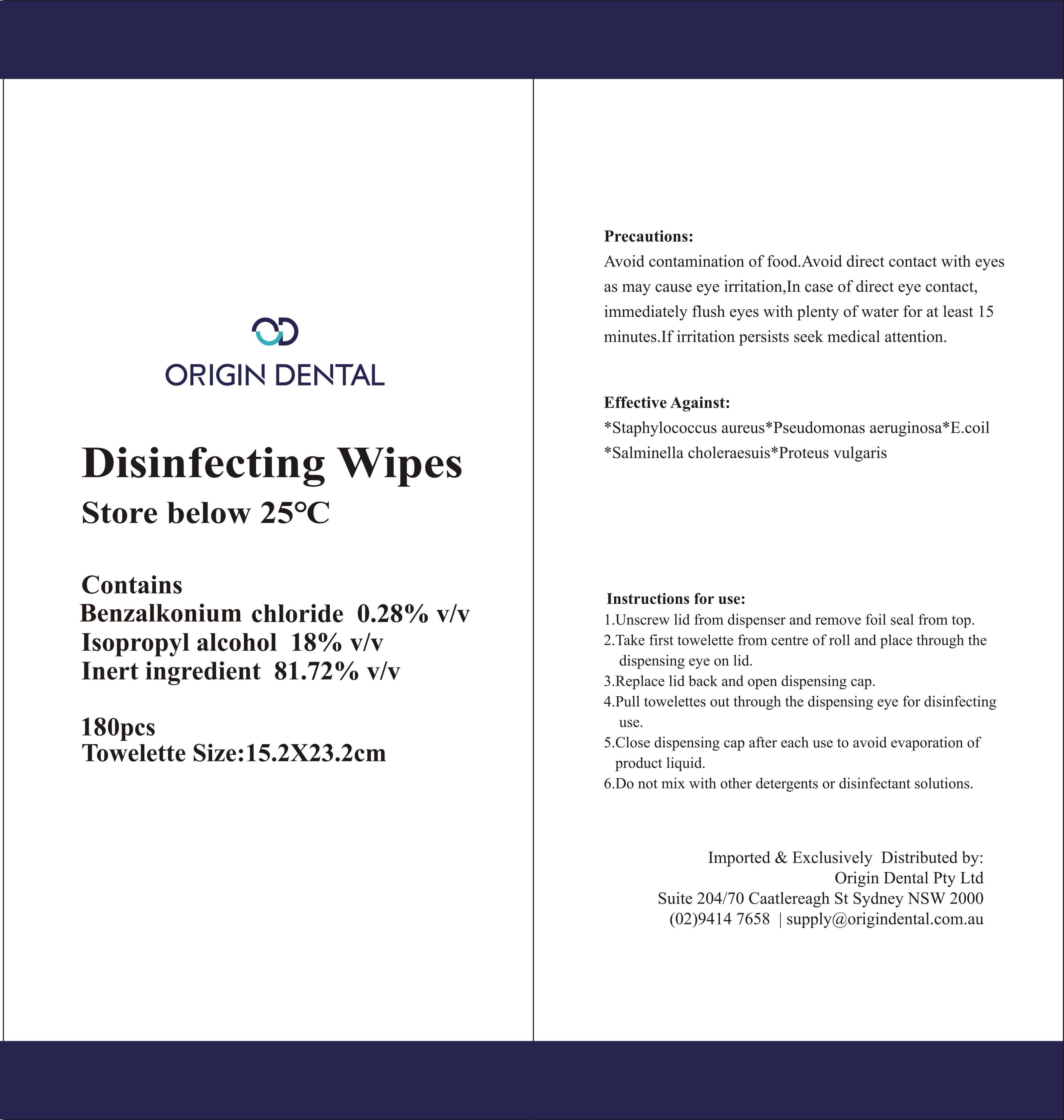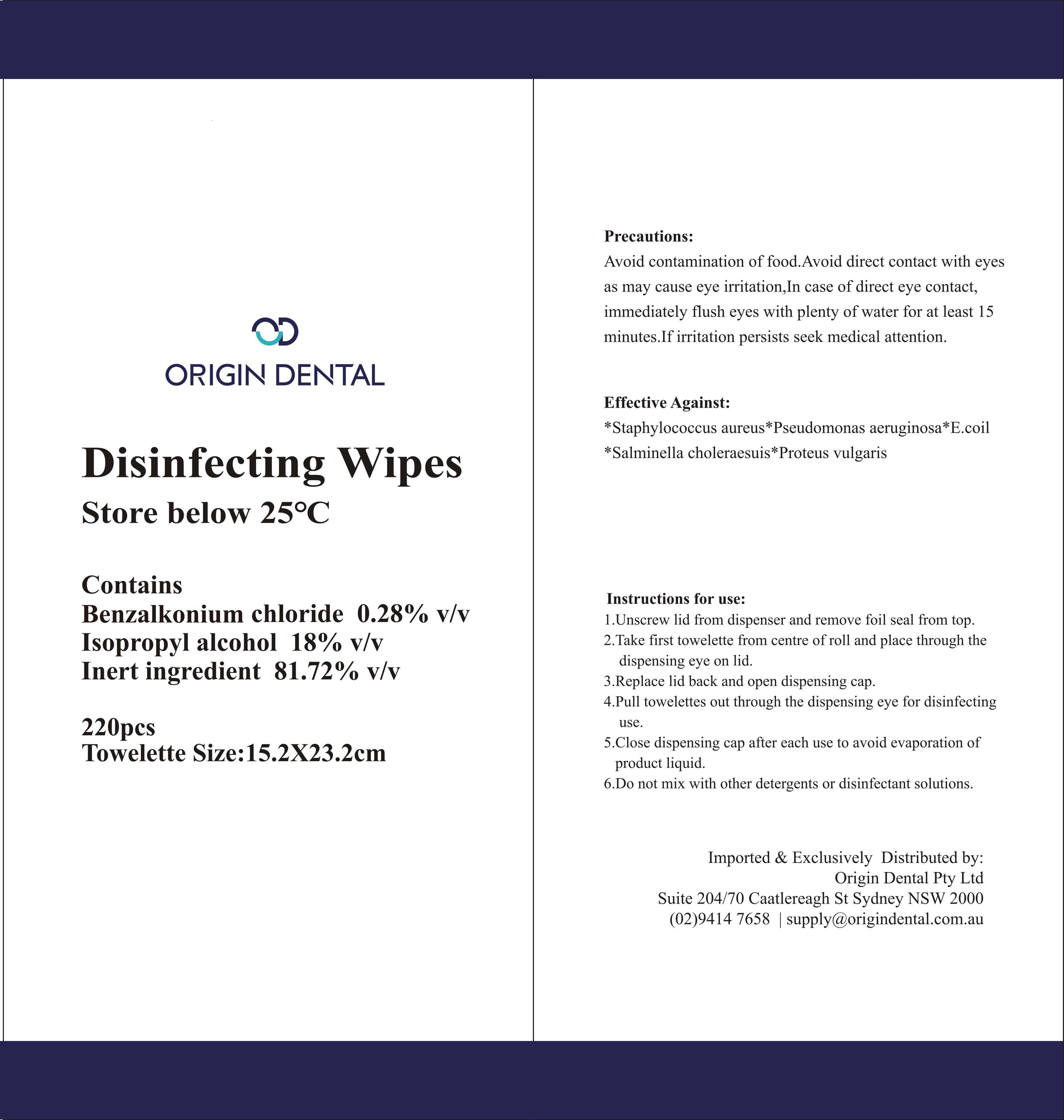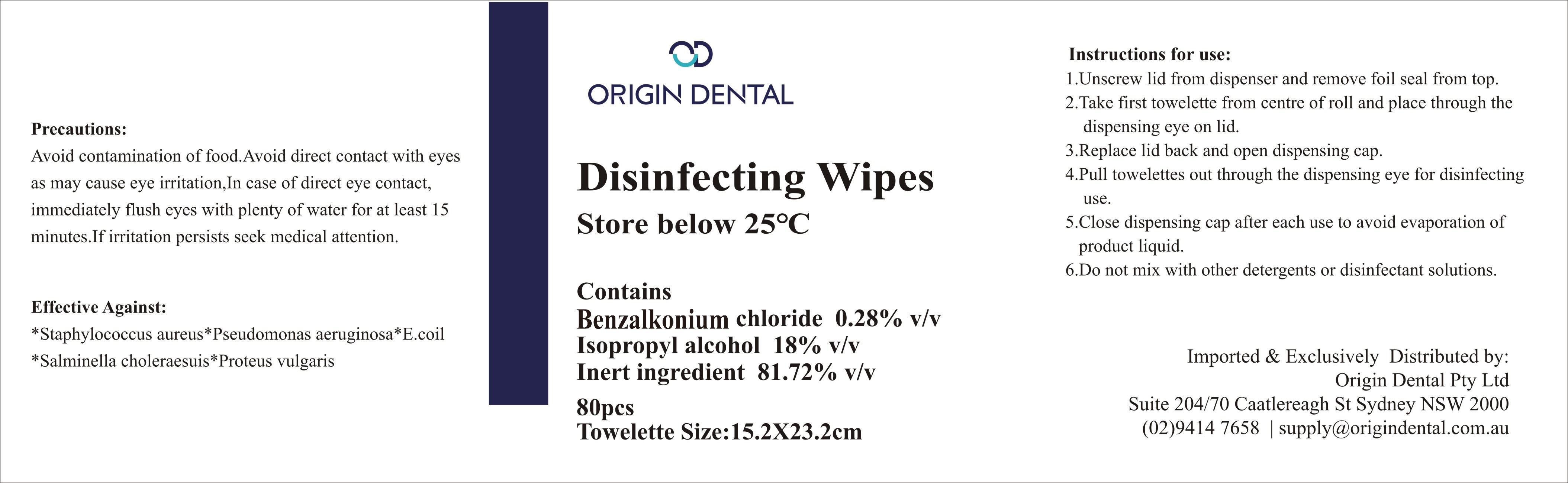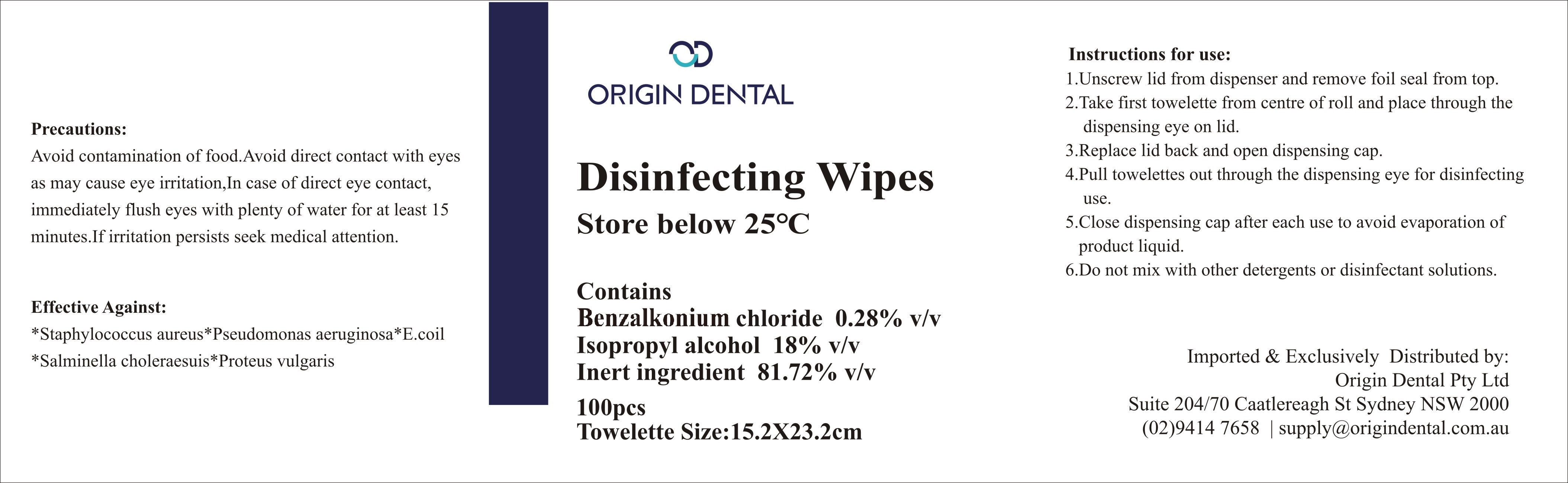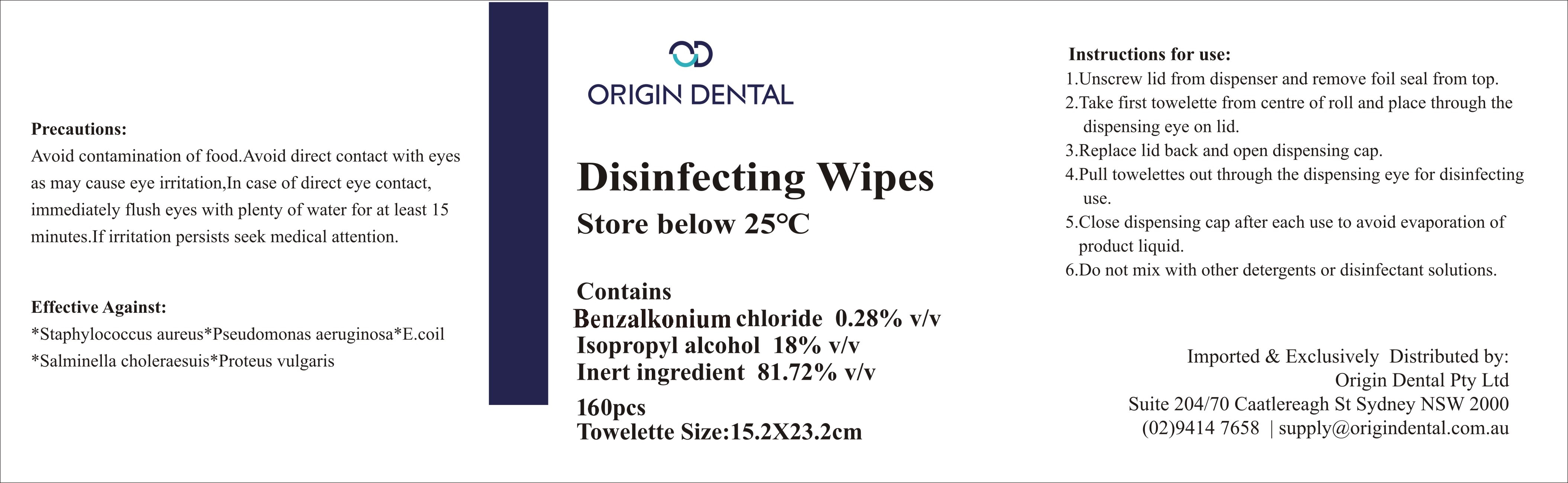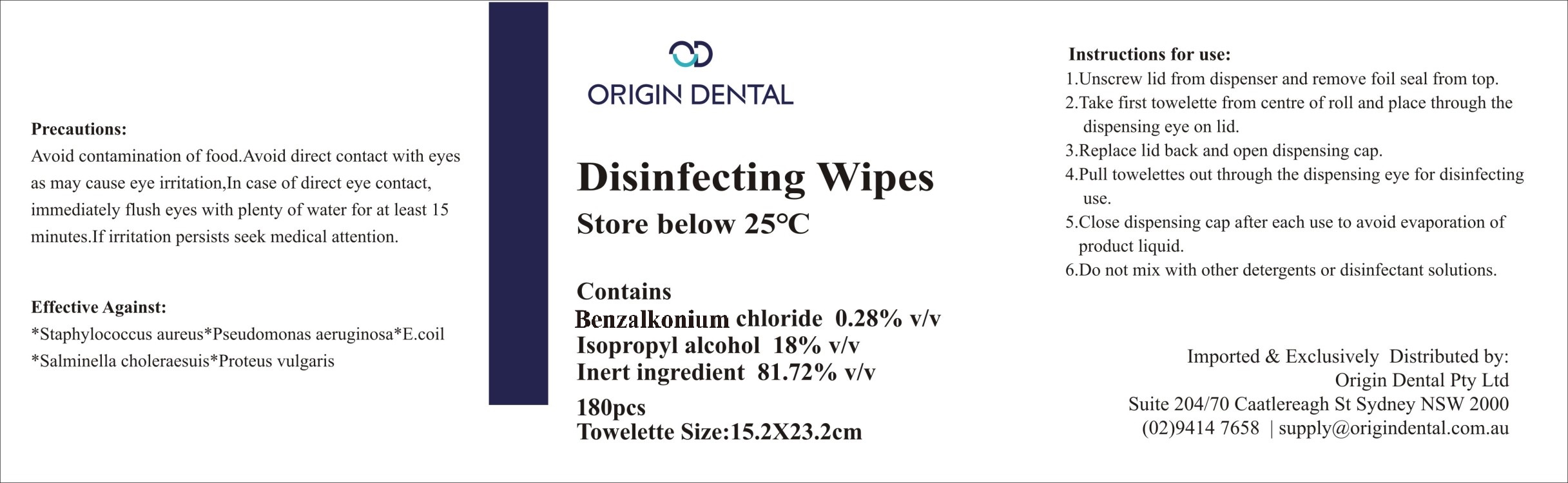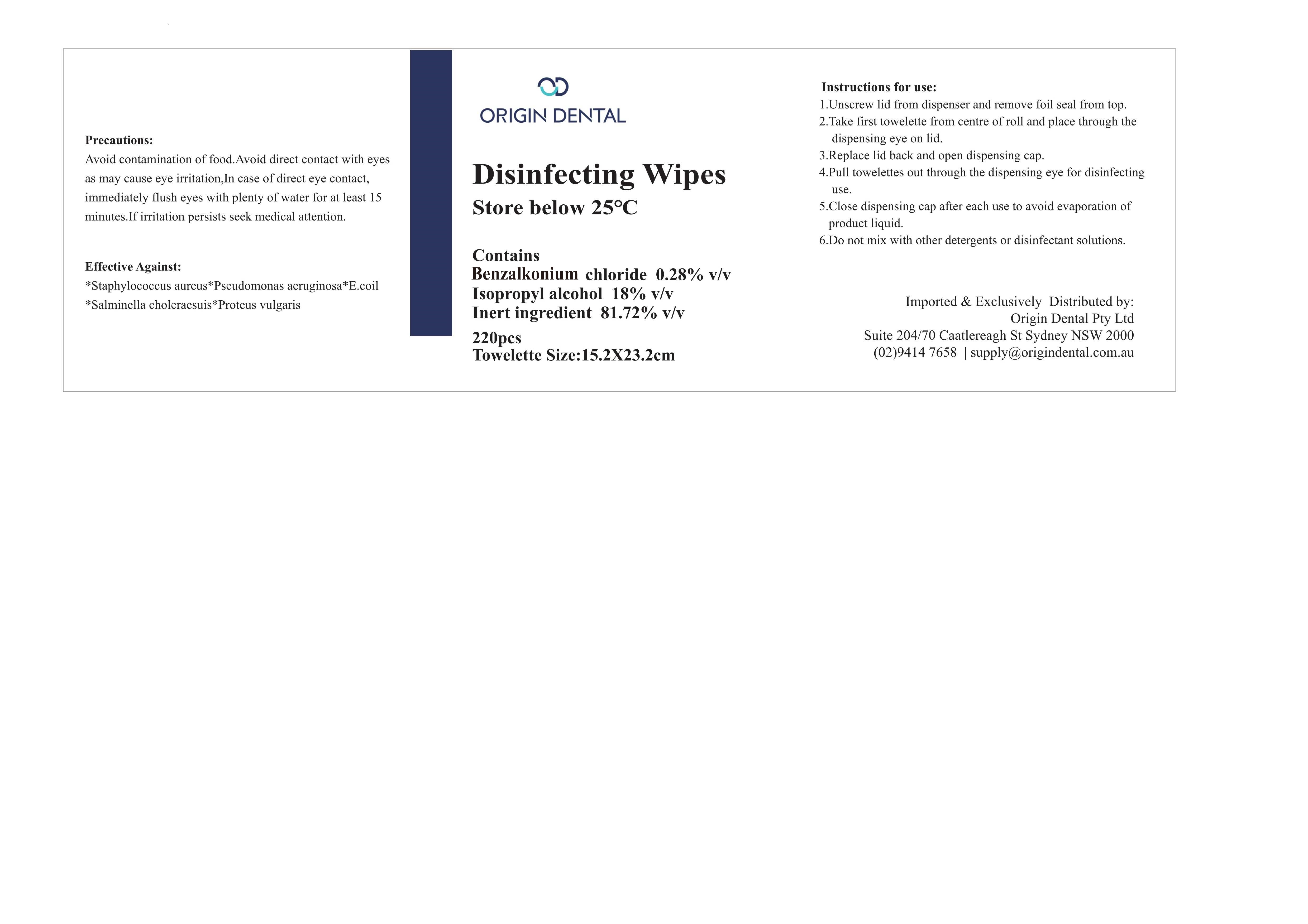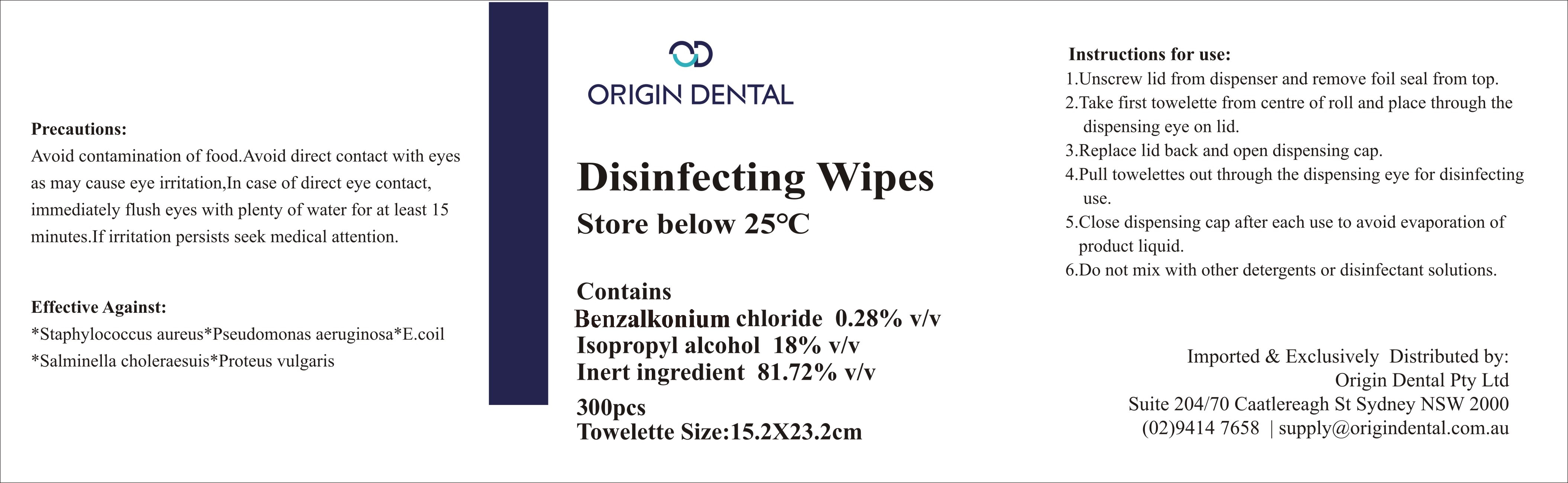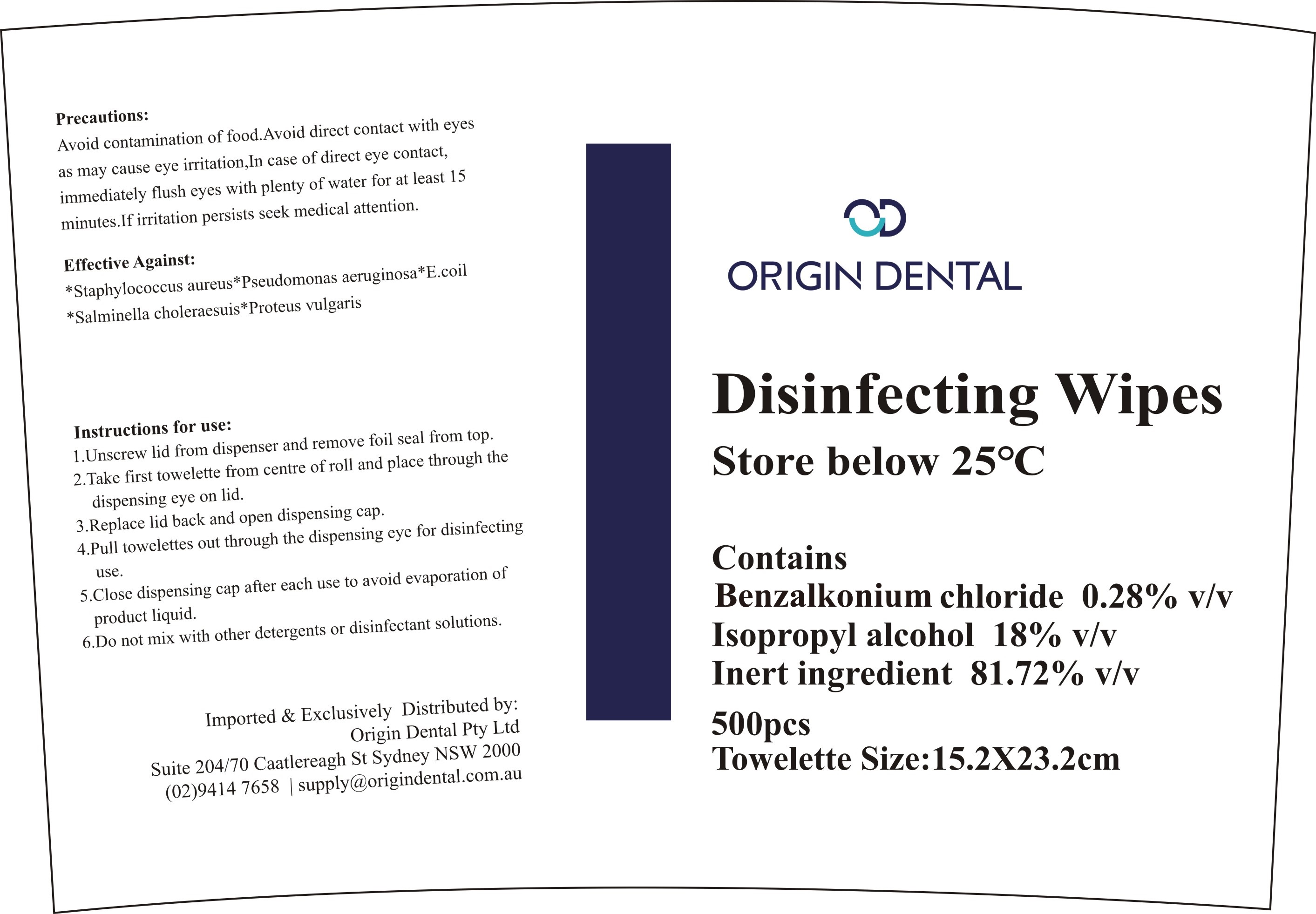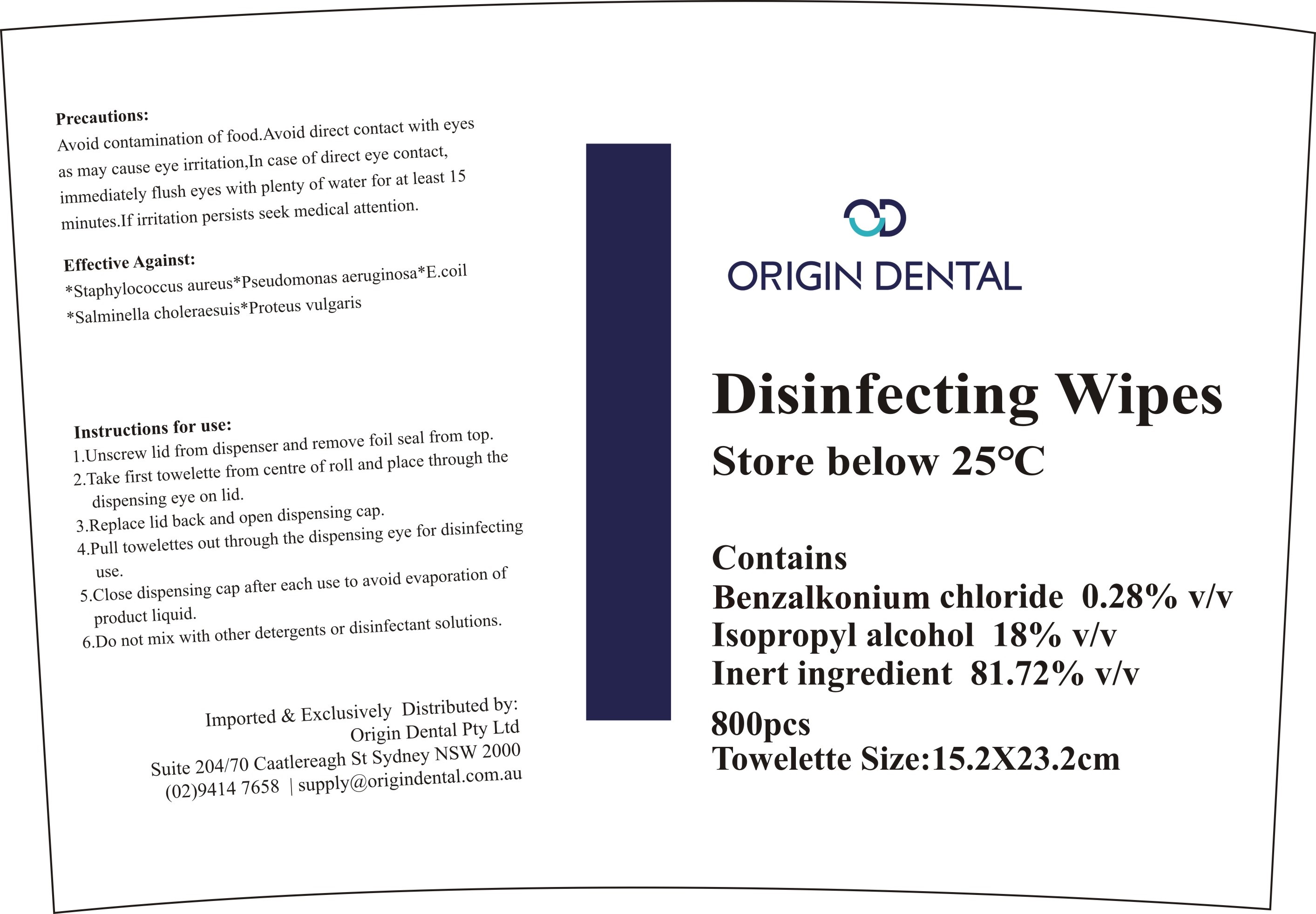 DRUG LABEL: ANTIBACTERIAL WIPES UNSCENTED
NDC: 80593-008 | Form: SOLUTION
Manufacturer: ZHANGZHOU WANSIKE ELECTRONICS CO., LTD
Category: otc | Type: HUMAN OTC DRUG LABEL
Date: 20210317

ACTIVE INGREDIENTS: BENZALKONIUM CHLORIDE 0.28 g/100 1
INACTIVE INGREDIENTS: WATER; ISOPROPYL ALCOHOL; PROPYLENE GLYCOL; PHENOXYETHANOL

80593-008
ANTIBACTERIAL WIPES UNSCENTED

Active Ingredient(s)

Benzalkonium Chloride 0.28%

Purpose

Effective Against：
*Staphylococcus aureus *Pseudomonas aeruginosa *E.coil
*Salmi nella choleraesuis *Proteus vulgaris

Use

Avoid contamination of food.Avoid direct contact with eyes as may cause eye irritation, In case of direct eye contact, immediately flush eyes with plenty of water for atleast 15 minutes.If irritation persists seek medical attention.

Warnings

1.Unscrew lid from dispenser and remove foil seal from top.
2.Take first towelette from centre of roll and place through the dispensing eye on lid.
3.Replace lid back and open dispensing cap.
4.Pull towelettes out through the dispensing eye for disinfecting use.
5.Close dispensing cap after each use to avoid evaporation of product liquid.
6.Do not mix with other detergents or disinfectant solutions.

Do not use

Do not mix with other detergents or disinfectant solutions.

WHEN USING

1.Unscrew lid from dispenser and remove foil seal from top.
2.Take first towelette from centre of roll and place through the dispensing eye on lid.
3.Replace lid back and open dispensing cap.
4.Pull towelettes out through the dispensing eye for disinfecting use.
5.Close dispensing cap after each use to avoid evaporation of product liquid.
6.Do not mix with other detergents or disinfectant solutions.

STOP USE

/

KEEP OUT OF REACH OF CHILDREN

/

Directions

Instructions for use：
1.Unscrew lid from dispenser and remove foil seal from top.
2.Take first towelette from centre of roll and place through the dispensing eye on lid.
3.Replace lid back and open dispensing cap.
4.Pull towelettes out through the dispensing eye for disinfecting use.
5.Close dispensing cap after each use to avoid evaporation of product liquid.
6.Do not mix with other detergents or disinfectant solutions.

Other information

/

Inactive ingredients

Isopropyl Alcohol 18%
Phenoxyethanol 0.3%
Propylene glycol 0.3%
Pure Water

Package Label - Principal Display Panel

80593-008-01 180 solution in 1 Bag

80593-008-02 220 solution in 1 Bag

80593-008-03 80 solution in 1 canister

80593-008-04 100 solution in 1 canister

80593-008-05 160 solution in 1 canister

80593-008-06 180 solution in 1 canister

80593-008-07 220 solution in 1 canister

80593-008-08 300 solution in 1 canister

80593-008-10 800 solution in 1 canister